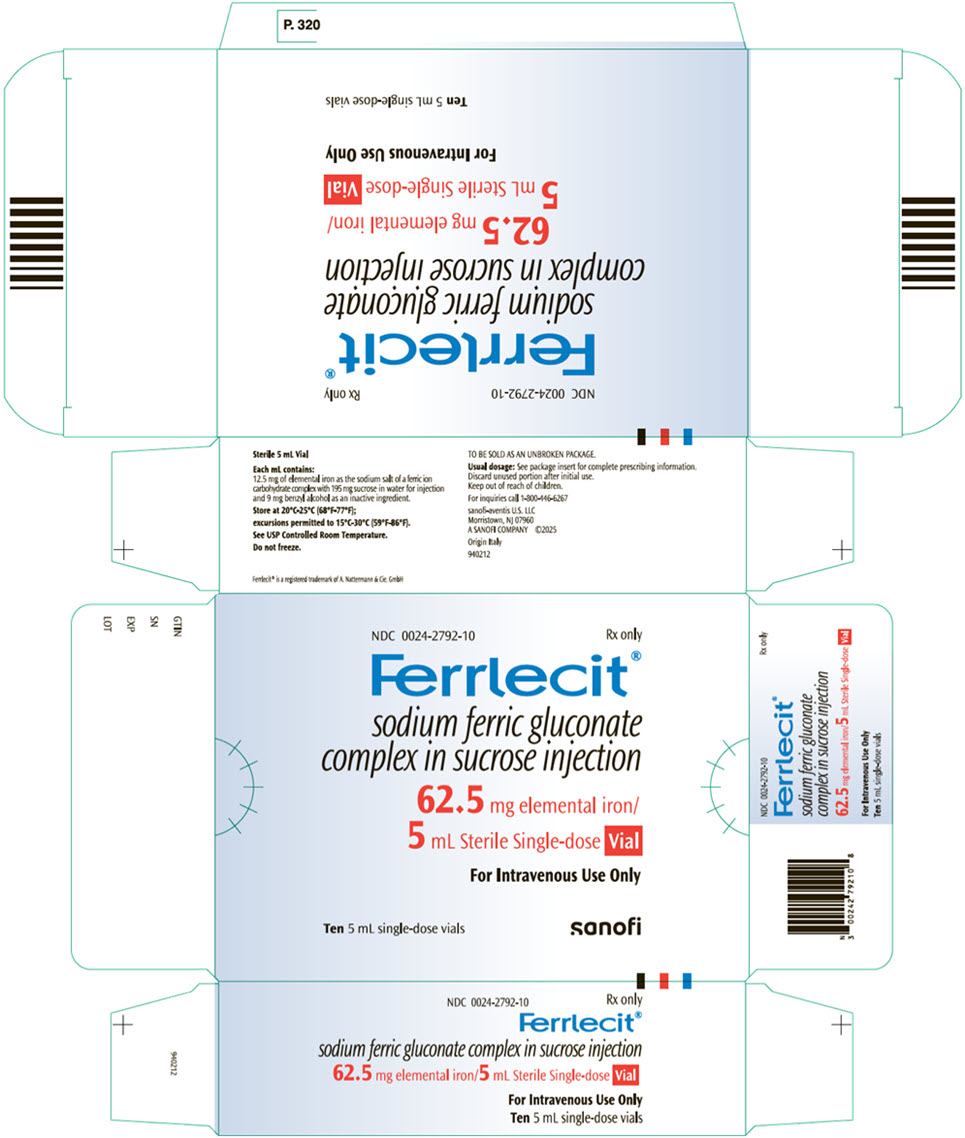 DRUG LABEL: Ferrlecit
NDC: 0024-2792 | Form: INJECTION
Manufacturer: sanofi-aventis  U.S. LLC
Category: prescription | Type: HUMAN PRESCRIPTION DRUG LABEL
Date: 20251007

ACTIVE INGREDIENTS: SODIUM FERRIC GLUCONATE COMPLEX 12.5 mg/1 mL
INACTIVE INGREDIENTS: BENZYL ALCOHOL 9 mg/1 mL; SUCROSE 195 mg/1 mL; WATER

HIGHLIGHTS OF PRESCRIBING INFORMATION

These highlights do not include all the information needed to use FERRLECIT® safely and effectively. See full prescribing information for FERRLECIT.
FERRLECIT (sodium ferric gluconate complex in sucrose), injection,
for intravenous use
Initial U.S. Approval: 1999

1 INDICATIONS AND USAGE

Ferrlecit is an iron replacement product for treatment of iron deficiency anemia in adult patients and in pediatric patients age 6 years and older with chronic kidney disease receiving hemodialysis who are receiving supplemental epoetin therapy. (1)

2 DOSAGE AND ADMINISTRATION

- Adult Patients - The recommended adult dosage is 10 mL (125 mg of elemental iron) diluted in 100 mL of 0.9% sodium chloride administered by intravenous infusion over 1 hour per dialysis session or undiluted as a slow intravenous injection (at a rate of up to 12.5 mg/min) per dialysis session. (2.2)
- Pediatric Patients - The recommended pediatric dosage is 0.12 mL/kg (1.5 mg/kg of elemental iron) diluted in 25 mL 0.9% sodium chloride and administered by intravenous infusion over 1 hour per dialysis session. (2.3)
- Do not mix Ferrlecit with other medications or add to parenteral nutrition solutions for intravenous infusion.
- Administer in 0.9% saline. (2)

3 DOSAGE FORMS AND STRENGTHS

Injection: 62.5 mg/5 mL (12.5 mg/mL) in single-dose vial. (3)

4 CONTRAINDICATIONS

Known hypersensitivity to sodium ferric gluconate or any of its inactive components. (4)

5 WARNINGS AND PRECAUTIONS

- Hypersensitivity Reactions: Monitor patients for signs and symptoms of hypersensitivity during and after Ferrlecit administration for at least 30 minutes and until clinically stable following completion of the infusion. Only administer Ferrlecit when personnel and therapies are immediately available for the treatment of anaphylaxis and other hypersensitivity reactions. (5.1)
- Hypotension: Ferrlecit may cause hypotension. Monitor patients for signs and symptoms of hypotension during and following each Ferrlecit dose. (5.2)
- Iron Overload: Regularly monitor hematologic responses during Ferrlecit therapy. Do not administer Ferrlecit to patients with iron overload. (5.3)
- Benzyl Alcohol Toxicity: Premature and low-birth-weight infants may be more likely to develop toxicity. (5.4)

6 ADVERSE REACTIONS

The most commonly reported adverse reactions (≥10%) in adult patients were nausea, vomiting and/or diarrhea, injection site reaction, hypotension, cramps, hypertension, dizziness, dyspnea, chest pain, leg cramps, and pain. In patients 6 to 15 years of age the most common adverse reactions (≥10%) were hypotension, headache, hypertension, tachycardia and vomiting. (6.1)

To report SUSPECTED ADVERSE REACTIONS, contact sanofi-aventis U.S. LLC at 1-800-633-1610 or FDA at 1-800-FDA-1088 or www.fda.gov/medwatch.

8 USE IN SPECIFIC POPULATIONS

- Pregnancy: Risk of hypersensitivity reaction which may have serious consequences for the fetus. Use only if clearly needed (contains benzyl alcohol). (8.1)
- Lactation: Not recommended when breastfeeding. (8.2)
- Pediatric Use: Safety and effectiveness have not been established in pediatric patients <6 years of age. (8.4)

FULL PRESCRIBING INFORMATION

1 INDICATIONS AND USAGE

Ferrlecit is indicated for the treatment of iron deficiency anemia in adult patients and in pediatric patients age 6 years and older with chronic kidney disease receiving hemodialysis who are receiving supplemental epoetin therapy.

2 DOSAGE AND ADMINISTRATION

2.1 Important Administration Instructions

The dosage of Ferrlecit is expressed in terms of mg of elemental iron. Each 5 mL sterile, single-dose vial contains 62.5 mg of elemental iron (12.5 mg/mL).

Do not mix Ferrlecit with other medications or add to parenteral nutrition solutions for intravenous infusion. The compatibility of Ferrlecit with intravenous infusion vehicles other than 0.9% sodium chloride has not been evaluated. Parenteral drug products should be inspected visually for particulate matter and discoloration before administration, whenever the solution and container permit. If diluted, use immediately.

Ferrlecit treatment may be repeated if iron deficiency reoccurs.

2.2 Adult Dosage and Administration

The recommended dosage of Ferrlecit for the repletion treatment of iron deficiency in hemodialysis patients is 10 mL of Ferrlecit (125 mg of elemental iron). Ferrlecit may be diluted in 100 mL of 0.9% sodium chloride administered by intravenous infusion over 1 hour per dialysis session. Ferrlecit may also be administered undiluted as a slow intravenous injection (at a rate of up to 12.5 mg/min) per dialysis session. For repletion treatment most patients may require a cumulative dose of 1000 mg of elemental iron administered over 8 dialysis sessions. Ferrlecit has been administered at sequential dialysis sessions by infusion or by slow intravenous injection during the dialysis session itself.

Data from Ferrlecit postmarketing spontaneous reports indicate that individual doses exceeding 125 mg may be associated with a higher incidence and/or severity of adverse events [see Adverse Reactions (6.2)].

2.3 Pediatric Dosage and Administration

The recommended pediatric dosage of Ferrlecit for the repletion treatment of iron deficiency in hemodialysis patients is 0.12 mL/kg Ferrlecit (1.5 mg/kg of elemental iron) diluted in 25 mL 0.9% sodium chloride and administered by intravenous infusion over 1 hour per dialysis session. The maximum dosage should not exceed 125 mg per dose.

3 DOSAGE FORMS AND STRENGTHS

Injection: 62.5 mg/5 mL (12.5 mg/mL) clear, dark brown liquid in single-dose vial

4 CONTRAINDICATIONS

Ferrlecit is contraindicated in patients with known hypersensitivity to sodium ferric gluconate or any of its components. Reactions have included anaphylaxis [see Warnings and Precautions (5.1)].

5 WARNINGS AND PRECAUTIONS

5.1 Hypersensitivity Reactions

Serious hypersensitivity reactions, including anaphylactic-type reactions, some of which have been life-threatening and fatal, have been reported in patients receiving Ferrlecit in postmarketing experience. Patients may present with shock, clinically significant hypotension, loss of consciousness, or collapse. Monitor patients for signs and symptoms of hypersensitivity during and after Ferrlecit administration for at least 30 minutes and until clinically stable following completion of the infusion. Only administer Ferrlecit when personnel and therapies are immediately available for the treatment of anaphylaxis and other hypersensitivity reactions [see Adverse Reactions (6)].

In the single-dose, postmarketing safety study one patient experienced a life-threatening hypersensitivity reaction (diaphoresis, nausea, vomiting, severe lower back pain, dyspnea, and wheezing for 20 minutes) following Ferrlecit administration. Among 1,097 patients who received Ferrlecit in this study, there were 9 patients (0.8%) who had an adverse reaction that, in the view of the investigator, precluded further Ferrlecit administration. These included one life-threatening reaction, six allergic reactions (including pruritus, facial flushing, chills, dyspnea/chest pain, and rash), and two other reactions (hypotension and nausea). Another 2 patients experienced (0.2%) allergic reactions not deemed to represent drug intolerance (nausea/malaise and nausea/dizziness) following Ferrlecit administration.

5.2 Hypotension

Ferrlecit may cause clinically significant hypotension. Hypotension associated with lightheadedness, malaise, fatigue, weakness or severe pain in the chest, back, flanks, or groin has been reported. These hypotensive reactions may or may not be associated with signs and symptoms of hypersensitivity reactions and usually resolve within one to two hours. In the single-dose safety study, postadministration hypotensive events were observed in 22/1,097 patients (2%) following Ferrlecit administration. Transient hypotension may occur during dialysis. Administration of Ferrlecit may augment hypotension caused by dialysis. Monitor patients for signs and symptoms of hypotension during and following Ferrlecit administration [see Adverse Reactions (6.1)].

5.3 Iron Overload

Excessive therapy with parenteral iron can lead to excess storage of iron with the possibility of iatrogenic hemosiderosis. Patients receiving Ferrlecit require periodic monitoring of hematologic and iron parameters (hemoglobin, hematocrit, serum ferritin, and transferrin saturation).

5.4 Risk of Serious Adverse Reactions in Infants Due to Benzyl Alcohol Preservative

Ferrlecit is not approved for use in neonates or infants. Serious and fatal adverse reactions including "gasping syndrome" can occur in neonates and low-birth-weight infants treated with benzyl alcohol–preserved drugs, including Ferrlecit. The "gasping syndrome" is characterized by central nervous system depression, metabolic acidosis, and gasping respirations. The minimum amount of benzyl alcohol at which serious adverse reactions may occur is not known (Ferrlecit contains 9 mg of benzyl alcohol per mL) [see Use in Specific Populations (8.4)].

6 ADVERSE REACTIONS

The following clinically significant adverse reactions are discussed in greater detail in other sections of the labeling:

- Hypersensitivity [see Contraindications (4) and Warnings and Precautions (5.1)]
- Hypotension [see Warnings and Precautions (5.2)]

6.1 Clinical Trials Experience

Because clinical studies are conducted under widely varying conditions, adverse reaction rates observed in the clinical studies of a drug cannot be directly compared to rates in the clinical studies of another drug and may not reflect the rates observed in practice.

The most commonly reported adverse reactions (≥10%) in adult patients were nausea, vomiting and/or diarrhea, injection site reaction, hypotension, cramps, hypertension, dizziness, abnormal erythrocytes (e.g., changes in morphology, color, or number of red blood cells), dyspnea, chest pain, leg cramps and pain. In patients 6 to 15 years of age the most common adverse reactions (≥10%) were hypotension, headache, hypertension, tachycardia and vomiting.

Studies A and B

In multiple dose Studies A and B (total 126 adult patients), the most frequent treatment emergent adverse reactions following Ferrlecit were:

Body as a Whole: injection site reaction (33%), chest pain (10%), pain (10%), asthenia (7%), headache (7%), fatigue (6%), fever (5%), malaise, infection, abscess, chills, rigors, carcinoma, flu-like syndrome, sepsis, lightheadedness, weakness.

Nervous System: cramps (25%), dizziness (13%), paresthesias (6%), agitation, somnolence, decreased level of consciousness.

Respiratory System: dyspnea (11%), coughing (6%), upper respiratory infections (6%), rhinitis, pneumonia.

Cardiovascular System: hypotension (29%), hypertension (13%), syncope (6%), tachycardia (5%), bradycardia, vasodilatation, angina pectoris, myocardial infarction, pulmonary edema.

Gastrointestinal System: nausea, vomiting and/or diarrhea (35%), anorexia, abdominal pain (6%), rectal disorder, dyspepsia, eructation, flatulence, gastrointestinal disorder, melena.

Musculoskeletal System: leg cramps (10%), myalgia, arthralgia, back pain, arm pain.

Skin and Appendages: pruritus (6%), rash, increased sweating.

Genitourinary System: urinary tract infection, and menorrhagia.

Special Senses: conjunctivitis, rolling of the eyes, watery eyes, puffy eye lids, arcus senilis, redness of the eye, diplopia, and deafness.

Metabolic and Nutritional Disorders: hyperkalemia (6%), generalized edema (5%), leg edema, peripheral edema, hypoglycemia, edema, hypervolemia, hypokalemia.

Hematologic System: abnormal erythrocytes (11%) (changes in morphology, color, or number of red blood cells), anemia, leukocytosis, lymphadenopathy.

Study C – Pediatric

Pediatric Patients: In a clinical trial of 66 iron-deficient pediatric hemodialysis patients, 6 to 15 years of age, inclusive, who were receiving a stable erythropoietin dosing regimen, the most common adverse reactions, occurring in ≥5%, regardless of treatment dosage, were: hypotension (35%), headache (24%), hypertension (23%), tachycardia (17%), vomiting (11%), fever (9%), nausea (9%), abdominal pain (9%), pharyngitis (9%), diarrhea (8%), infection (8%), rhinitis (6%), and thrombosis (6%). More patients in the higher dose group (3.0 mg/kg) than in the lower dose group (1.5 mg/kg) experienced the following adverse events: hypotension (41% vs. 28%), tachycardia (21% vs. 13%), fever (15% vs. 3%), headache (29% vs. 19%), abdominal pain (15% vs. 3%), nausea (12% vs. 6%), vomiting (12% vs. 9%), pharyngitis (12% vs. 6%), and rhinitis (9% vs. 3%).

6.2 Postmarketing Experience

In the single-dose, postmarketing, safety study, 11% of patients who received Ferrlecit and 9.4% of patients who received placebo reported adverse reactions. The most frequent adverse reactions following Ferrlecit administration were: hypotension (2%), nausea, vomiting and/or diarrhea (2%), pain (0.7%), hypertension (0.6%), allergic reaction (0.5%), chest pain (0.5%), pruritus (0.5%), and back pain (0.4%). The following additional events were reported in two or more patients: hypertonia, nervousness, dry mouth, and hemorrhage.

In the multiple-dose, open-label surveillance study, 28% of the patients received concomitant angiotensin-converting enzyme inhibitor (ACEI) therapy. The incidences of both drug intolerance and suspected allergic events following first dose Ferrlecit administration were 1.6% in patients with concomitant ACEI use compared to 0.7% in patients without concomitant ACEI use. The patient with a life-threatening event was not on ACEI therapy. One patient had facial flushing immediately on Ferrlecit exposure. No hypotension occurred and the event resolved rapidly and spontaneously without intervention other than drug withdrawal.

Because these reactions are reported voluntarily from a population of uncertain size, it is not always possible to reliably estimate their frequency or establish a causal relationship to drug exposure.

The following additional adverse reactions have been identified with the use of Ferrlecit from postmarketing spontaneous reports:

Cardiovascular System: shock, fetal bradycardia, injection site superficial thrombophlebitis, phlebitis, acute myocardial ischemia with or without myocardial infarction or with in-stent thrombosis in the context of a hypersensitivity reaction.

Gastrointestinal System: dysgeusia.

Immune System: anaphylactic-type reactions.

Nervous System: loss of consciousness, generalized convulsion, hypoesthesia.

Skin and Appendages: skin discoloration, pallor.

Individual doses exceeding 125 mg may be associated with a higher incidence and/or severity of adverse events based on information from postmarketing spontaneous reports. These adverse events included hypotension, nausea, vomiting, abdominal pain, diarrhea, dizziness, dyspnea, urticaria, chest pain, paresthesia, and peripheral swelling.

7 DRUG INTERACTIONS

Drug-drug interactions involving Ferrlecit have not been studied. Ferrlecit may reduce the absorption of concomitantly administered oral iron preparations.

8 USE IN SPECIFIC POPULATIONS

8.1 Pregnancy

Risk Summary

Parenteral iron administration may be associated with hypersensitivity reactions [see Warnings and Precautions (5.1)], which may have serious consequences, such as fetal bradycardia (see Clinical Considerations). Advise pregnant women of the potential risk to the fetus. Available data from postmarketing reports with Ferrlecit use in pregnancy are insufficient to assess the risk of major birth defects and miscarriage.

Ferrlecit contains benzyl alcohol as a preservative. Because benzyl alcohol is rapidly metabolized by a pregnant woman, benzyl alcohol exposure in the fetus is unlikely. However, adverse reactions have occurred in premature neonates and low-birth-weight infants who received intravenously administered benzyl alcohol–containing drugs [see Warnings and Precautions (5.4) and Use in Specific Populations (8.4)]. Consider alternative iron replacement therapies without benzyl alcohol.

There are risks to the mother and fetus associated with untreated iron deficiency anemia in pregnancy (see Clinical Considerations).

In the absence of maternal toxicity, Ferrlecit was not teratogenic to offspring of pregnant mice or rats at clinically relevant exposures (see Data).

The estimated background risk of major birth defects and miscarriage for the indicated population is unknown. All pregnancies have a background risk of birth defects, loss, or other adverse outcomes. In the U.S. general population, the estimated background risk of major birth defects and miscarriage in clinically recognized pregnancies is 2%–4% and 15%–20%, respectively.

Clinical Considerations

Disease-associated maternal and/or embryo/fetal risk

Untreated iron deficiency anemia (IDA) in pregnancy is associated with adverse maternal outcomes such as postpartum anemia. Adverse pregnancy outcomes associated with IDA include increased risk for preterm delivery and low birth weight.

Fetal/Neonatal adverse reactions

Severe adverse reactions including circulatory failure (severe hypotension, shock including in the context of anaphylactic reaction) may occur in pregnant women with intravenous iron administration, which may have serious consequences on the fetus such as fetal bradycardia, especially during the second and third trimesters.

Data

Animal data

Ferrlecit was administered intravenously to pregnant mice during gestation days 6 to 15 at doses of 5, 30, and 100 mg Fe/kg/day to assess embryofetal development. No teratogenic effects were seen in offspring at the highest dose, representing maternal exposure of approximately 4 times maximum human exposure based on body surface area. There were increased fetal resorptions and decreased fetal weights at doses that caused maternal toxicity as evidenced by decreased body-weight gain and decreased food consumption.

Ferrlecit was administered intravenously to pregnant rats during gestation days 6 to 15 at doses of 4 and 20 mg Fe/kg/day to assess embryofetal development. No teratogenic effects were seen in offspring at the highest dose, representing maternal exposure of approximately 1.5 times maximum human exposure based on body surface area. There were decreases in gestation index and litter size, increased fetal resorptions, and decreased fetal weights at doses that caused maternal toxicity as evidenced by decreased body-weight gain and decreased food consumption.

8.2 Lactation

Risk Summary

Ferrlecit contains benzyl alcohol. Because benzyl alcohol is rapidly metabolized by a lactating woman, benzyl alcohol exposure in the breastfed infant is unlikely. However, adverse reactions have occurred in premature neonates and low-birth-weight infants who received intravenously administered benzyl alcohol–containing drugs [see Warnings and Precautions (5.4) and Use in Specific Populations (8.4)]. Consider alternative iron replacement therapies without benzyl alcohol for use during lactation.

There are no available data on the presence of Ferrlecit in human or animal milk, the effects on milk production, or the effects on the breastfed child.

8.4 Pediatric Use

The safety and effectiveness of Ferrlecit have been established in pediatric patients 6 to 15 years of age [see Dosage and Administration (2.3), Clinical Pharmacology (12.3), and Clinical Studies (14)]. Safety and effectiveness in pediatric patients younger than 6 years of age have not been established.

Benzyl Alcohol Toxicity and Pediatrics

Ferrlecit is not approved for use in neonates or infants. Serious adverse reactions including fatal reactions and the "gasping syndrome" occurred in premature neonates and low-birth-weight infants in the neonatal intensive care unit who received drugs containing benzyl alcohol as a preservative. In these cases, benzyl alcohol dosages of 99 to 234 mg/kg/day produced high levels of benzyl alcohol and its metabolites in the blood and urine (blood levels of benzyl alcohol were 0.61 to 1.378 mmol/L). Additional adverse reactions included gradual neurological deterioration, seizures, intracranial hemorrhage, hematologic abnormalities, skin breakdown, hepatic and renal failure, hypotension, bradycardia, and cardiovascular collapse. Benzyl alcohol contained in Ferrlecit may cause serious and anaphylactoid reactions in infants and children up to 3 years old. The administration of medications containing benzyl alcohol to newborns or premature neonates has been associated with a fatal "gasping syndrome" (symptoms include a striking onset of gasping syndrome, hypotension, bradycardia, and cardiovascular collapse). Preterm, low-birth-weight infants may be more likely to develop these reactions because they could be less able to metabolize benzyl alcohol. The minimum amount of benzyl alcohol at which serious adverse reactions may occur is not known (Ferrlecit contains 9 mg of benzyl alcohol per mL) [see Warnings and Precautions (5.4)].

8.5 Geriatric Use

Clinical studies of Ferrlecit did not include sufficient numbers of subjects aged 65 and over to determine whether they respond differently from younger subjects. Other reported clinical experience has not identified differences in responses between the elderly and younger patients. In general, dose selection for an elderly patient should be cautious, usually starting at the low end of the dosing range, reflecting the greater frequency of decreased hepatic, renal, or cardiac function, and of concomitant disease or other drug therapy.

10 OVERDOSAGE

The Ferrlecit iron complex is not dialyzable.

No data is available regarding overdose of Ferrlecit in humans. Excessive dosages of Ferrlecit may lead to accumulation of iron in storage sites potentially leading to hemosiderosis. Do not administer Ferrlecit to patients with iron overload [see Warnings and Precautions (5.3)].

Individual doses exceeding 125 mg may be associated with a higher incidence and/or severity of adverse events [see Adverse Reactions (6.2)].

Ferrlecit at elemental iron doses of 125 mg/kg, 78.8 mg/kg, 62.5 mg/kg and 250 mg/kg caused deaths in mice, rats, rabbits, and dogs respectively. The major symptoms of acute toxicity were decreased activity, staggering, ataxia, increases in the respiratory rate, tremor, and convulsions.

11 DESCRIPTION

Ferrlecit® (sodium ferric gluconate complex in sucrose injection), an iron replacement product, is a stable macromolecular complex with an apparent molecular weight on gel chromatography of 289,000–440,000 daltons. The macromolecular complex is negatively charged at alkaline pH and is present in solution with sodium cations. The product has a deep red color indicative of ferric oxide linkages. The chemical name is D-Gluconic acid, iron (3+) sodium salt.

The structural formula is considered to be [NaFe2O3(C6H11O7)(C12H22011)5]n≈200•

Ferrlecit is supplied as a clear, dark brown liquid in colorless glass vials. Each sterile, single-dose vial of 5 mL of Ferrlecit for intravenous injection contains 62.5 mg (12.5 mg/mL) of elemental iron as the sodium salt of a ferric ion carbohydrate complex in an alkaline aqueous solution with approximately 20% sucrose w/v (195 mg/mL) in water for injection, pH 7.7–9.7.

Each mL contains 9 mg of benzyl alcohol as an inactive ingredient.

12 CLINICAL PHARMACOLOGY

12.1 Mechanism of Action

Ferrlecit is used to replete the body content of iron. Iron is critical for normal hemoglobin synthesis to maintain oxygen transport. Additionally, iron is necessary for metabolism and various enzymatic processes.

12.3 Pharmacokinetics

Multiple sequential single-dose intravenous pharmacokinetic studies were performed on 14 healthy iron-deficient volunteers. Entry criteria included hemoglobin ≥10.5 gm/dL and transferrin saturation ≤15% (TSAT) or serum ferritin value ≤20 ng/mL. In the first stage, each subject was randomized 1:1 to undiluted Ferrlecit injection of either 125 mg/hr or 62.5 mg/0.5 hr (2.1 mg/min). Five days after the first stage, each subject was re-randomized 1:1 to undiluted Ferrlecit injection of either 125 mg/7 min or 62.5 mg/4 min (>15.5 mg/min).

Peak drug levels (Cmax) varied significantly by dosage and by rate of administration with the highest Cmax observed in the regimen in which 125 mg was administered in 7 minutes (19.0 mg/L). The terminal elimination half-life for drug bound iron was approximately 1 hour. Half-life varied by dose but not by rate of administration. Half-life values were 0.85 and 1.45 hours for the 62.5 mg/4 min and 125 mg/7 min regimens, respectively. Total clearance of Ferrlecit was 3.02 to 5.35 L/h. The AUC for Ferrlecit bound iron varied by dose from 17.5 mg-h/L (62.5 mg) to 35.6 mg-h/L (125 mg). Approximately 80% of drug bound iron was delivered to transferrin as a mononuclear ionic iron species within 24 hours of administration in each dosage regimen. Direct movement of iron from Ferrlecit to transferrin was not observed. Mean peak transferrin saturation returned to near baseline by 40 hours after administration of each dosage regimen.

Pediatrics: Single-dose intravenous pharmacokinetic analyses were performed on 48 iron-deficient pediatric hemodialysis patients. Twenty-two patients received 1.5 mg/kg Ferrlecit and 26 patients received 3.0 mg/kg Ferrlecit (maximum dose 125 mg). The mean Cmax, AUC0–∞, and terminal elimination half-life values following a 1.5 mg/kg dose were 12.9 mg/L, 95.0 mg∙hr/L, and 2.0 hours, respectively. The mean Cmax, AUC0–∞, and terminal elimination half-life values following a 3.0 mg/kg dose were 22.8 mg/L, 170.9 mg∙hr/L, and 2.5 hours, respectively.

In vitro experiments have shown that less than 1% of the iron species within Ferrlecit can be dialyzed through membranes with pore sizes corresponding to 12,000 to 14,000 daltons over a period of up to 270 minutes. Human studies in renally competent patients suggest the clinical insignificance of urinary excretion.

13 NONCLINICAL TOXICOLOGY

13.1 Carcinogenesis, Mutagenesis, Impairment of Fertility

Long term carcinogenicity studies of sodium ferric gluconate in animals were not performed.

Sodium ferric gluconate was not genotoxic in the Ames test or the rat micronucleus test. Sodium ferric gluconate produced a clastogenic effect in an in vitro chromosomal aberration assay in Chinese hamster ovary cells.

Studies to assess the effects of sodium ferric gluconate on fertility were not conducted.

14 CLINICAL STUDIES

Two clinical studies (Studies A and B) were conducted in adults and one clinical study was conducted in pediatric patients (Study C) to assess the efficacy and safety of Ferrlecit.

Study A

Study A was a three-center, randomized, open-label study of the safety and efficacy of two doses of Ferrlecit administered intravenously to iron-deficient hemodialysis patients. The study included both a dose-response concurrent control and an historical control. Enrolled patients received a test dose of Ferrlecit (25 mg of elemental iron) and were then randomly assigned to receive Ferrlecit at cumulative doses of either 500 mg (low dose) or 1000 mg (high dose) of elemental iron. Ferrlecit was given to both dose groups in eight divided doses during sequential dialysis sessions (a period of 16 to 17 days). At each dialysis session, patients in the low-dose group received Ferrlecit 62.5 mg of elemental iron over 30 minutes, and those in the high-dose group received Ferrlecit 125 mg of elemental iron over 60 minutes. The primary endpoint was the change in hemoglobin from baseline to the last available observation through Day 40.

Eligibility for this study included chronic hemodialysis patients with a hemoglobin below 10 g/dL (or hematocrit at or below 32%) and either serum ferritin below 100 ng/mL or transferrin saturation below 18%. Exclusion criteria included significant underlying disease or inflammatory conditions or an epoetin requirement of greater than 10,000 units three times per week. Parenteral iron and red cell transfusion were not allowed for two months before the study. Oral iron and red cell transfusion were not allowed during the study for Ferrlecit-treated patients.

The historical control population consisted of 25 chronic hemodialysis patients who received only oral iron supplementation for 14 months and did not receive red cell transfusion. All patients had stable epoetin doses and hematocrit values for at least two months before initiation of oral iron therapy.

The evaluated population consisted of 39 patients in the low-dose Ferrlecit (sodium ferric gluconate complex in sucrose injection) group (50% female, 50% male; 74% white, 18% black, 5% Hispanic, 3% Asian; mean age 54 years, range 22–83 years), 44 patients in the high-dose Ferrlecit group (50% female, 48% male, 2% unknown; 75% white, 11% black, 5% Hispanic, 7% other, 2% unknown; mean age 56 years, range 20–87 years), and 25 historical control patients (68% female, 32% male; 40% white, 32% black, 20% Hispanic, 4% Asian, 4% unknown; mean age 52 years, range 25–84 years).

The mean baseline hemoglobin and hematocrit were similar between treatment and historical control patients: 9.8 g/dL and 29% and 9.6 g/dL and 29% in low- and high-dose Ferrlecit-treated patients, respectively, and 9.4 g/dL and 29% in historical control patients. Baseline serum transferrin saturation was 20% in the low-dose group, 16% in the high-dose group, and 14% in the historical control. Baseline serum ferritin was 106 ng/mL in the low-dose group, 88 ng/mL in the high-dose group, and 606 ng/mL in the historical control.

Patients in the high-dose Ferrlecit group achieved significantly higher increases in hemoglobin and hematocrit than patients in the low-dose Ferrlecit group. See Table 1.

Table 1: Study A: Hemoglobin, Hematocrit, and Iron Studies
 | Mean Change from Baseline to Two Weeks after Cessation of Therapy
 | Ferrlecit 1000 mg IV (N=44) | Ferrlecit 500 mg IV (N=39) | Historical Control Oral Iron (N=25)
Hemoglobin (g/dL) | 1.1 [p<0.01 versus the 500 mg group.] | 0.3 | 0.4
Hematocrit (%) | 3.6 | 1.4 | 0.8
Transferrin Saturation (%) | 8.5 | 2.8 | 6.1
Serum Ferritin (ng/mL) | 199 | 132 | NA

Study B

Study B was a single-center, non-randomized, open-label, historically controlled, study of the safety and efficacy of variable, cumulative doses of intravenous Ferrlecit in iron-deficient hemodialysis patients. Ferrlecit administration was identical to Study A. The primary efficacy variable was the change in hemoglobin from baseline to the last available observation through Day 50.

Inclusion and exclusion criteria were identical to those of Study A as was the historical control population. Sixty-three patients were evaluated in this study: 38 in the Ferrlecit-treated group (37% female, 63% male; 95% white, 5% Asian; mean age 56 years, range 22–84 years) and 25 in the historical control group (68% female, 32% male; 40% white, 32% black, 20% Hispanic, 4% Asian, 4% unknown; mean age 52 years, range 25–84 years).

Ferrlecit-treated patients were considered to have completed the study per protocol if they received at least eight Ferrlecit doses of either 62.5 mg or 125 mg of elemental iron. A total of 14 patients (37%) completed the study per protocol. Twelve (32%) Ferrlecit-treated patients received less than eight doses, and 12 (32%) patients had incomplete information on the sequence of dosing. Not all patients received Ferrlecit at consecutive dialysis sessions and many received oral iron during the study.

Cumulative Ferrlecit Dose (mg of elemental iron) | 62.5 | 250 | 375 | 562.5 | 625 | 750 | 1000 | 1125 | 1187.5
Patients (#) | 1 | 1 | 2 | 1 | 10 | 4 | 12 | 6 | 1

Baseline hemoglobin and hematocrit values were similar between the treatment and control groups, and were 9.1 g/dL and 27.3%, respectively, for Ferrlecit-treated patients. Serum iron studies were also similar between treatment and control groups, with the exception of serum ferritin, which was 606 ng/mL for historical control patients, compared to 77 ng/mL for Ferrlecit-treated patients.

In this patient population, only the Ferrlecit-treated group achieved increase in hemoglobin and hematocrit from baseline. See Table 2.

Table 2: Study B: Hemoglobin, Hematocrit, and Iron Studies
 | Mean Change from Baseline to One Month after Treatment
 | Ferrlecit (N=38) Change | Oral Iron (N=25) Change
Hemoglobin (g/dL) | 1.3 | 0.4
Hematocrit (%) | 3.8 | 0.2
Transferrin Saturation (%) | 6.7 | 1.7
Serum Ferritin (ng/dL) | 73 | -145

Study C

Study C was a multicenter, randomized, open-label study of the safety and efficacy of two Ferrlecit dose regimens (1.5 mg/kg or 3.0 mg/kg of elemental iron) administered intravenously to 66 iron-deficient (transferrin saturation <20% and/or serum ferritin <100 ng/mL) pediatric hemodialysis patients, 6 to 15 years of age, inclusive who were receiving a stable erythropoietin dosing regimen.

Ferrlecit at a dose of 1.5 mg/kg or 3.0 mg/kg (up to a maximum dose of 125 mg of elemental iron) in 25 mL 0.9% sodium chloride was infused intravenously over 1 hour during each hemodialysis session for eight sequential dialysis sessions. Thirty-two patients received the 1.5 mg/kg dosing regimen (47% male, 53% female; 66% Caucasian, 25% Hispanic, and 3% Black, Asian, or Other; mean age 12.3 years). Thirty-four patients received the 3.0 mg/kg dosing regimen (56% male, 44% female; 77% Caucasian, 12% Hispanic, 9% Black, and 3% Other; mean age 12.0 years).

The primary endpoint was the change in hemoglobin concentration from baseline to 2 weeks after last Ferrlecit administration. There was no significant difference between the treatment groups. Improvements in hematocrit, transferrin saturation, serum ferritin, and reticulocyte hemoglobin concentrations compared to baseline values were observed 2 weeks after the last Ferrlecit infusion in both the 1.5 mg/kg and 3.0 mg/kg treatment groups (Table 3).

Table 3: Study C: Hemoglobin, Hematocrit, and Iron Status
 | Mean Change from Baseline to Two Weeks after Cessation of Therapy in Patients Completing Treatment
 | 1.5 mg/kg Ferrlecit (N=25) | 3.0 mg/kg Ferrlecit (N=32)
Hemoglobin (g/dL) | 0.8 | 0.9
Hematocrit (%) | 2.6 | 3.0
Transferrin Saturation (%) | 5.5 | 10.5
Serum Ferritin (ng/mL) | 192 | 314
Reticulocyte Hemoglobin Content (pg) | 1.3 | 1.2

The increased hemoglobin concentrations were maintained at 4 weeks after the last Ferrlecit infusion in both the 1.5 mg/kg and the 3.0 mg/kg Ferrlecit dose treatment groups.

16 HOW SUPPLIED/STORAGE AND HANDLING

How Supplied

Ferrlecit is a clear, dark brown liquid supplied in colorless glass vials. Each sterile, single-dose vial contains 62.5 mg of elemental iron in 5 mL for intravenous use. Discard unused portion.

Carton containing 10 vials: NDC 0024-2792-10

Storage

Store at 20°C–25°C (68°F–77°F); excursions permitted to 15°C–30°C (59°F–86°F). See USP Controlled Room Temperature. Do not freeze.

Keep out of the reach of children.

17 PATIENT COUNSELING INFORMATION

Prior to Ferrlecit administration:

- Question patients regarding any prior history of reactions to parenteral iron products.
- Advise patients of the risks associated with Ferrlecit.
- Advise patients to report adverse reactions associated with the use of Ferrlecit, including hypersensitivity, allergic reactions, chest pain, dizziness, lightheadedness, swelling, and breathing problems [see Warnings and Precautions (5.1, 5.2) and Adverse Reactions (6.1, 6.2)].

Advise patients that Ferrlecit may reduce the absorption of concomitantly administered oral iron preparations [see Drug Interactions (7)].

Pregnancy

Advise pregnant women about the risk of hypersensitivity reactions which may have serious consequences for the fetus. Advise patients who may become pregnant to inform their healthcare provider of a known or suspected pregnancy (contains benzyl alcohol) [see Use in Specific Populations (8.1)].

Lactation

Advise patients that treatment with Ferrlecit is not recommended for use while breastfeeding [see Use in Specific Populations (8.2)].

sanofi-aventis U.S. LLC
Morristown, NJ 07960
A SANOFI COMPANY

©2025 sanofi-aventis U.S. LLC
Ferrlecit is a registered trademark of A. Nattermann & Cie. GmbH

PRINCIPAL DISPLAY PANEL - 5 mL Vial Carton

NDC 0024-2792-10

Rx only

Ferrlecit®

sodium ferric gluconate
complex in sucrose injection

62.5 mg elemental iron/
5 mL Sterile Single-dose Vial

For Intravenous Use Only

Ten 5 mL single-dose vials

sanofi